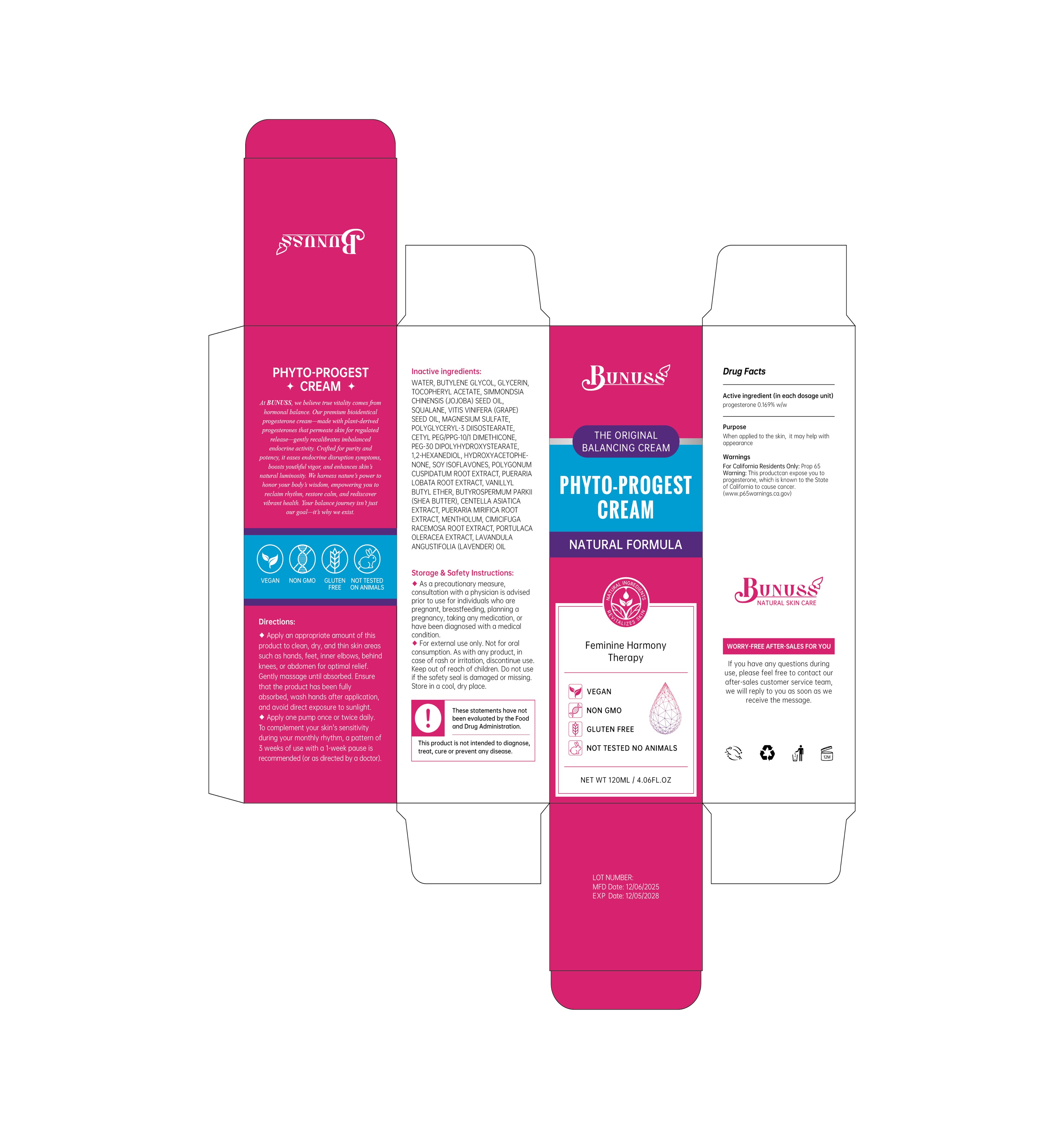 DRUG LABEL: BUNUSS Phyto-Pro Skin Cream
NDC: 84867-030 | Form: PASTE
Manufacturer: Jiashen International Trade Limited
Category: otc | Type: HUMAN OTC DRUG LABEL
Date: 20251201

ACTIVE INGREDIENTS: PROGESTERONE 16.9 mg/1 mL
INACTIVE INGREDIENTS: VANILLYL BUTYL ETHER; MENTHOL, UNSPECIFIED FORM; PUERARIA MONTANA VAR. LOBATA ROOT; CENTELLA ASIATICA TRITERPENOIDS; PURSLANE; POLYGONUM CUSPIDATUM ROOT; POLYGLYCERYL-3 DIISOSTEARATE; VITIS VINIFERA (GRAPE) SEED OIL; 1,2-HEXANEDIOL; CETYL PEG/PPG-10/1 DIMETHICONE (HLB 3.7); BUTYLENE GLYCOL; GLYCERIN; SQUALANE; CIMICIFUGA RACEMOSA ROOT; LAVANDULA ANGUSTIFOLIA (LAVENDER) OIL; PEG-30 DIPOLYHYDROXYSTEARATE; SOY ISOFLAVONES; BUTYROSPERMUM PARKII (SHEA) BUTTER; PUERARIA MIRIFICA ROOT; SIMMONDSIA CHINENSIS (JOJOBA) SEED OIL; MAGNESIUM SULFATE; .ALPHA.-TOCOPHEROL ACETATE; WATER

ACTIVE INGREDIENT

Progesterone

PURPOSE

When applied to the skin, it may help with appearance

KEEP OUT OF REACH OF CHILDREN

INDICATIONS AND USAGE

Apply an appropriate amount of thisproduct to clean, dry, and thin skin areassuch as hands, feet, inner elbows, behindknees, or abdomen for optimal relief.Gently massage until absorbed. Ensurethat the product has been fullyabsorbed, wash hands after application,and avoid direct exposure to sunlight

DOSAGE AND ADMINISTRATION

Apply one pump once or twice daily.To complement your skin's sensitivityduring your monthly rhythm, a pattern of3 weeks of use with a 1-week pause isrecommended (or as directed by a doctor)

WARNINGS

Storage & Safety Instructions:As a precautionary measure,consultation with a physician is advisedprior to use for individuals who arepregnant, breastfeeding, planning apregnancy, taking any medication, orhave been diagnosed with a medicalcondition.For external use only. Not for oralconsumption. As with any product, incase of rash or irritation, discontinue use.Keep out of reach of children. Do not useif the safety seal is damaged or missing.Store in a cool, dry place.

INACTIVE INGREDIENT

WATER
BUTYLENE GLYCOL
GLYCERIN
TOCOPHERYL ACETATE
SIMMONDSIA CHINENSIS (JOJOBA) SEED OIL
SQUALANE
VITIS VINIFERA (GRAPE) SEED OIL
MAGNESIUM SULFATE
POLYGLYCERYL-3 DIISOSTEARATE
CETYL PEG/PPG-10/1 DIMETHICONE
PEG-30 DIPOLYHYDROXYSTEARATE
1,2-HEXANEDIOL
SOY ISOFLAVONES
POLYGONUM CUSPIDATUM ROOT EXTRACT
PUERARIA LOBATA ROOT EXTRACT
VANILLYL BUTYL ETHER
BUTYROSPERMUM PARKII (SHEA BUTTER)
CENTELLA ASIATICA EXTRACT
PUERARIA MIRIFICA ROOT EXTRACT
MENTHOLUM
CIMICIFUGA RACEMOSA ROOT EXTRACT
PORTULACA OLERACEA EXTRACT
LAVANDULA ANGUSTIFOLIA (LAVENDER) OIL